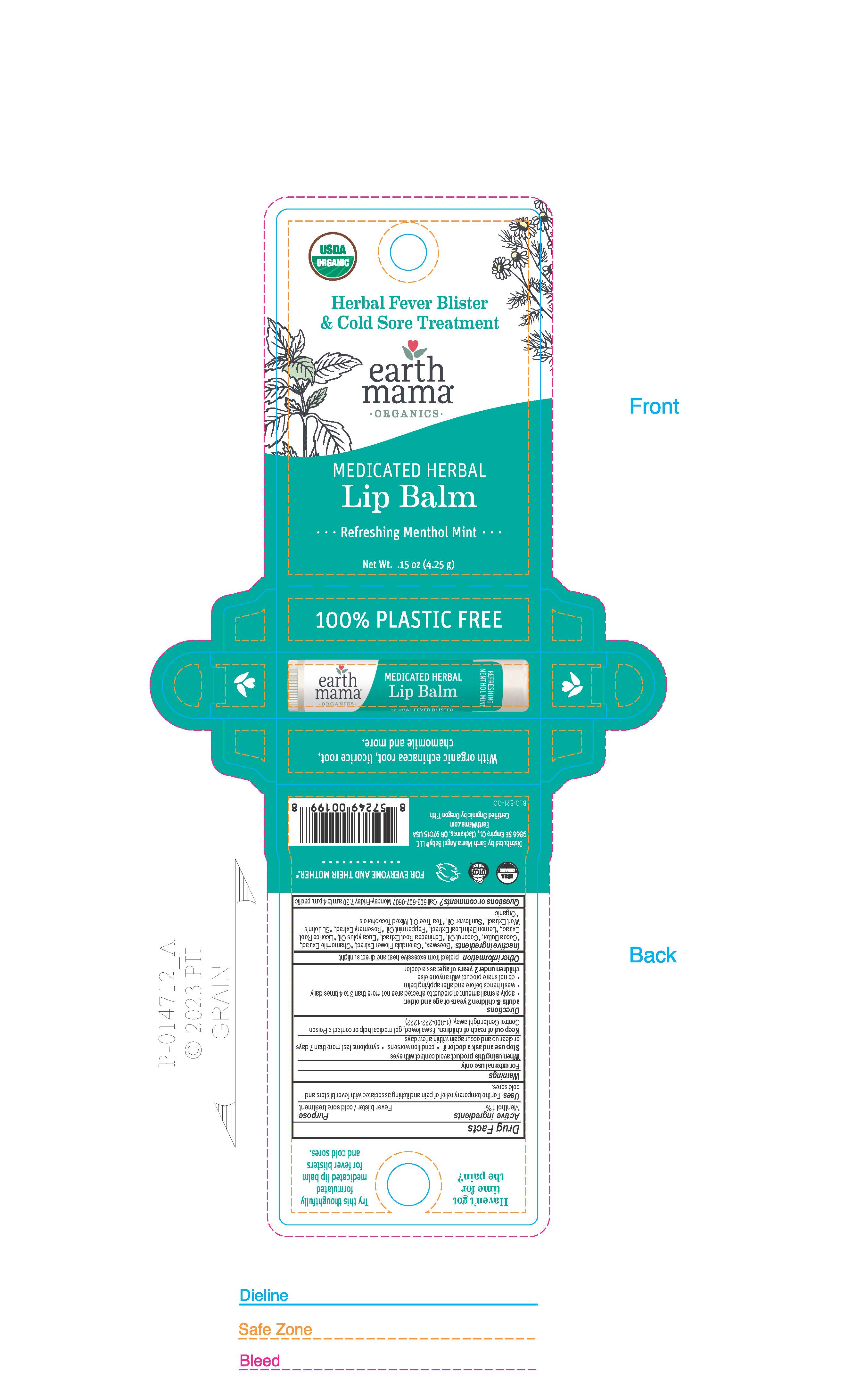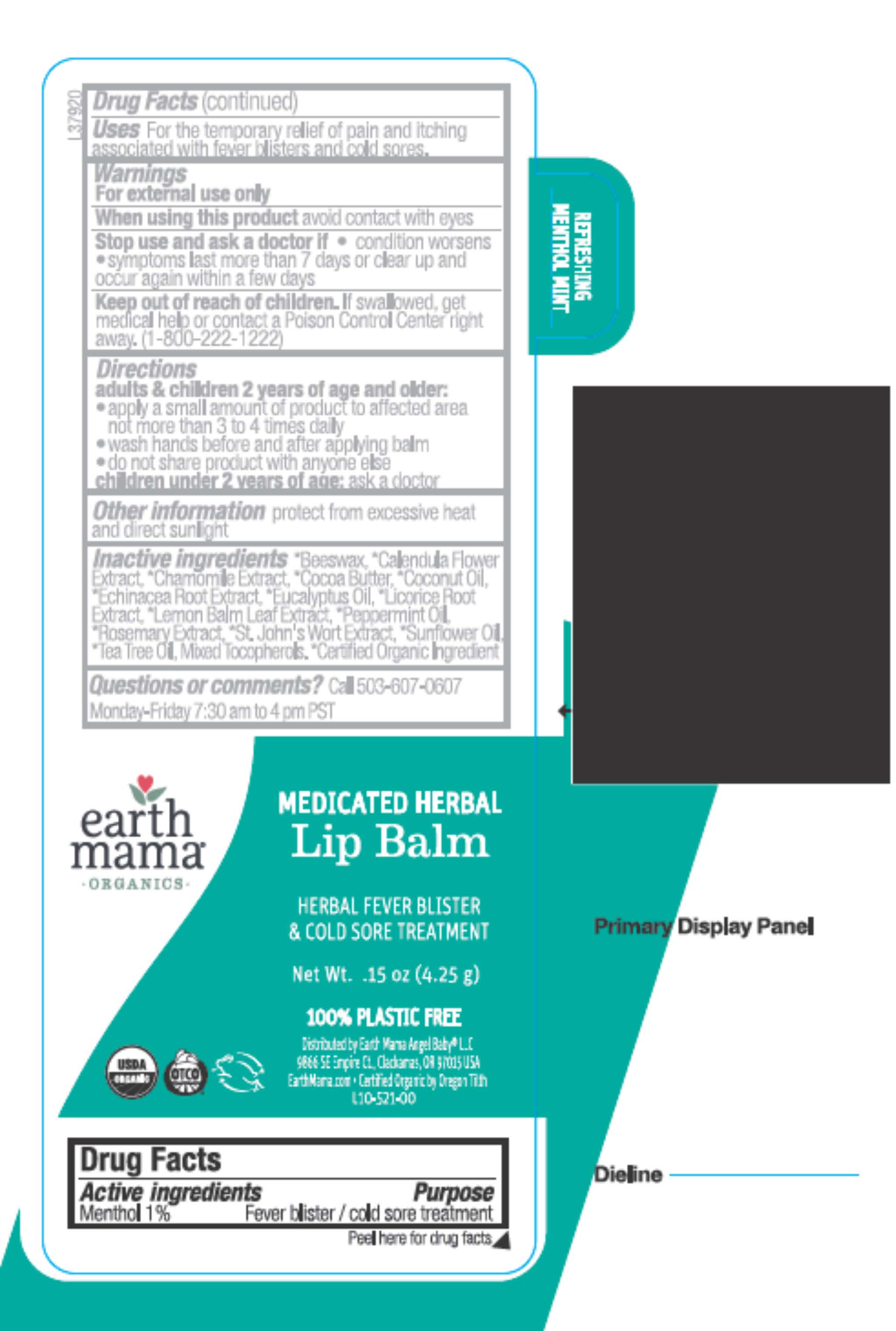 DRUG LABEL: Medicated Herbal Lip Balm
NDC: 72812-155 | Form: STICK
Manufacturer: Earth Mama Angel Baby LLC
Category: otc | Type: HUMAN OTC DRUG LABEL
Date: 20241001

ACTIVE INGREDIENTS: MENTHOL 0.0425 g/4.25 g
INACTIVE INGREDIENTS: SUNFLOWER OIL; TEA TREE OIL; CHAMOMILE FLOWER OIL; COCOA BUTTER; ROSEMARY OIL; PEPPERMINT OIL; COCONUT OIL; TOCOPHEROL; CALENDULA OFFICINALIS FLOWER; YELLOW WAX; MELISSA OFFICINALIS LEAF OIL; EUCALYPTUS OIL; ECHINACEA ANGUSTIFOLIA ROOT; ST. JOHN'S WORT; LICORICE

93760 Earth Mama Menthol Medicated Herbal Lip Balm

Active Ingredients

Menthol 1%

Purpose

Fever blister / cold sore treatment

INDICATIONS AND USAGE

UsesFor the temporary relief of pain and itching associated with fever blisters and

cold sores.

Warnings

For external use only

When using this productavoid contact with eyes

Stop use and ask a doctor if

- condition worsens
- symptoms last more than 7 days or clear up and occur again within a few days

Keep out of reach of children.If swallowed, get medical help or contact a Poison Control Center right away. (1-800-222-1222)

Directions

adults & children 2 years of age and older:

- apply a small amount of product to affected area not more than 3 to 4 times daily
- wash hands before and after applying balm
- do not share product with anyone else

children under 2 years of age:ask a doctor

STORAGE AND HANDLING

Other informationprotect from excessive heat and direct sunlight

INACTIVE INGREDIENT

Inactive ingredients*Beeswax, *Calendula Flower Extract, *Chamomile Extract, *Cocoa Butter, *Coconut Oil, *Echinacea Root Extract, *Eucalyptus Oil, *Licorice Root Extract, *Lemon Balm Leaf Extract, *Peppermint Oil, *Rosemary Extract, *St John's Wort Extract, *Sunflower Oil, *Tea Tree Oil, Mixed Tocopherols. *Organic

Questions or Comments?Call 503-607-0607 Monday-Friday 7:30 a.m to 4 p.m. pacific

Carton Text

Herbal Fever Blister

& Cold Sore Treatment

earth

mama

ORGANICS

MEDICATED HERBAL

Lip Balm

Refreshing Menthol Mint

Net Wt 0.15 Oz (4.25 g)

100% PLASTIC FREE

Haven't got

time for

the pain?

Try this thoughtfully

formulated

medicated lip balm

for fever blisters

and cold sores.

FOR EVERYONE AND THEIR MOTHER

Distributed by Earth Mama Angel Baby LLC

9866 SE Empire Ct., Clackamas, OR 97015 USA

EarthMama.com

Certified Organic by Oregon Tilth

B10-521-00

With Organic echinacea root, licorice root, chamomile and more.

Label Text

earth mama

ORGANICS

MEDICATED HERBAL

Lip Balm

HERBAL FEVER BLISTER

& COLD SORE TREATMENT

Net Wt 0.15 Oz (4.25 g)

100% PLASTIC FREE

Distributed by Earth Mama Angel Baby LLC

9866 SE Empire Ct., Clackamas, OR 97015 USA

EarthMama.com

Certified Organic by Oregon Tilth

L10-521-00

Refreshing Menthol Mint